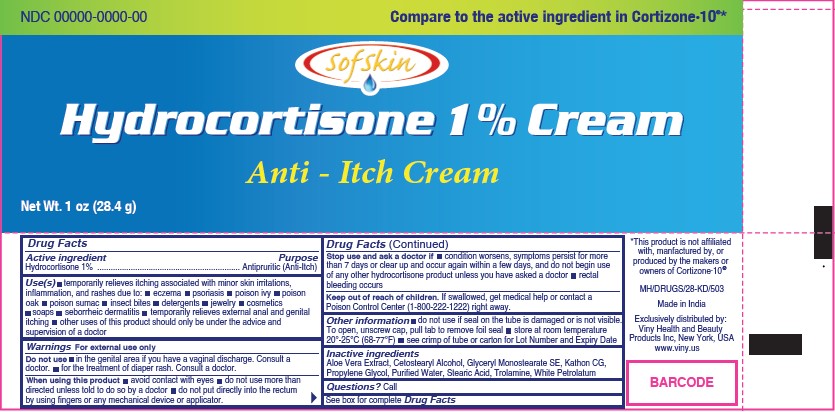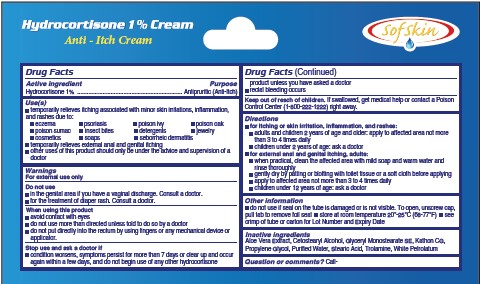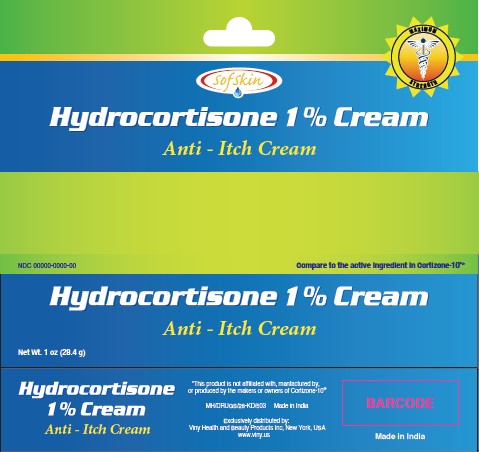 DRUG LABEL: SOFSKIN HYDROCORTISONE 1 PERCENT
NDC: 61040-129 | Form: CREAM
Manufacturer: GOPALDAS VISRAM AND COMPANY LIMITED
Category: otc | Type: HUMAN OTC DRUG LABEL
Date: 20241210

ACTIVE INGREDIENTS: HYDROCORTISONE 1 g/100 g
INACTIVE INGREDIENTS: CETOSTEARYL ALCOHOL; ALOE VERA LEAF; WHITE PETROLATUM; GLYCERYL STEARATE SE; WATER; STEARIC ACID; TROLAMINE; METHYLCHLOROISOTHIAZOLINONE/METHYLISOTHIAZOLINONE MIXTURE; PROPYLENE GLYCOL

Gopaldas (as CMO) - SOFSKIN HYDROCORTISONE CREAM 1% (61040-129)

ACTIVE INGREDIENTS

HYDROCORTISONE 1%

PURPOSE

Antipruritic (Anti-Itch)

USES

- temporarily relieves itching associated with minor skin irritations, inflammation, and rashes due to:
- eczema
- psoriasis
- poison ivy
- poison oak
- poison sumac
- insect bites
- detergents
- jewelry
- cosmetics
- soaps
- seborrheic dermatitis
- temporarily relieves external anal and genital itching
- other uses of this product should only be under the advice and supervision of a doctor

WARNINGS

- For external use only.

Do not use

- in the genital area if you have a vaginal discharge. Consult a doctor.
- for the treatment of diaper rash. Consult a doctor.

When using this product

- avoid contact with eyes
- do not use more than directed unless told to do so by a doctor
- do not put directly into the rectum by using fingers or any mechanical device or applicator.

Stop use and ask a doctor if

- condition worsens, symptoms persist for more than 7 days or clear up and occur again within a few days, and do not begin use
  of any other hydrocortisone product unless you have asked a doctor
- rectal bleeding occurs

Keep out of reach of children. If swallowed, get medical help or contact a Poison Control Center (1-800-222-1222) right away.

DIRECTIONS

- for itching or skin irritation, inflammation, and rashes:
- adults and children 2 years of age and older: apply to affected area not more than 3 to 4 times daily
- children under 2 years of age: ask a doctor
- for external anal and genital itching, adults:
- when practical, clean the affected area with mild soap and warm water and rinse thoroughly
- gently dry by patting or blotting with toilet tissue or a soft cloth before applying
- apply to affected area not more than 3 to 4 times daily
- children under 12 years of age: ask a doctor

OTHER INFORMATION

- do not use if seal on the tube is damaged or is not visible
- to open, unscrew cap, pull tab to remove foil seal
- store at 20° to 25°C (68° to 77°F)
- avoid excessive heat and humidity
- see crimp of tube or carton for Lot Number and Expiry Date

INACTIVE INGREDIENT

Aloe Vera Extract, Cetostearyl Alcohol, Glyceryl Monostearate SE, Kathon CG, Propylene Glycol, Purified Water, Stearic Acid, Trolamine, White Petrolatum